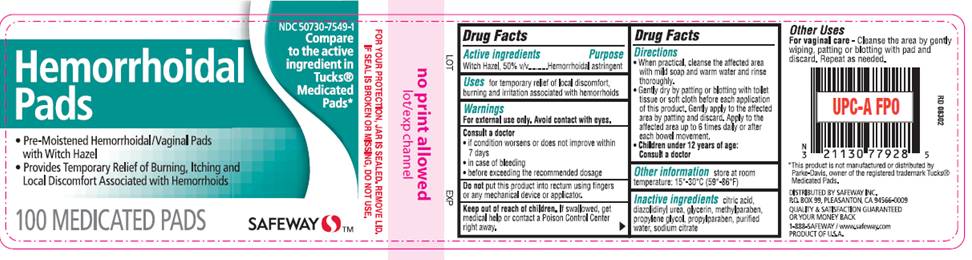 DRUG LABEL: Medicated Pad
NDC: 50730-7549 | Form: SOLUTION
Manufacturer: H and P Industries, Inc. dba Triad Group
Category: otc | Type: HUMAN OTC DRUG LABEL
Date: 20091208

ACTIVE INGREDIENTS: witch hazel .5 mL/1 mL
INACTIVE INGREDIENTS: citric acid monohydrate; diazolidinylurea; glycerin; methylparaben; propylene glycol; propylparaben; sodium citrate; water

DRUG FACTS

ACTIVE INGREDIENT

Witch Hazel 50% v/v

PURPOSE

Hemorrhoidal Astringent

USES

For temporary relief of local discomfort, burning, and irritation associated with hemorrhoids

WARNINGS

For external use only. Avoid contact with eyes.

Consult a doctor

- if condition worsens or does not improve within 7 days
- in case of bleeding
- before exceeding the recommended dosage

Do not

put this product into rectum using fingers or any mechanical device or applicator

Keep out of reach of children

If swallowed, get medical help or contact a Poison Control Center right away.

DIRECTIONS

- When practical, cleanse the affected area with mild soap and warm water and rinse thoroughly.
- Gently dry by patting or blotting with toilet tissue or soft cloth before each application of this product. Gently apply to the affected area by patting and then discard. Apply to the affected area up to 6 times daily or after each bowel movement.
- Children under 12 years of age: consult a doctor.

OTHER INFORMATION

Store at room temperature: 15°- 30° C (59° - 86° F)

OTHER USES

For vaginal care - Cleanse the area by gently wiping, patting or blotting with pad and discard. Repeat as needed.

INACTIVE INGREDIENTS

citric acid, diazolidinyl urea, glycerin, methylparaben, propylene glycol, propylparaben, purified water, sodium citrate

LABEL INFORMATION

NDC 50730-7549-1
Compare to the active ingredient in TUCKS®.
Hemorrhoidal
Pads

- Pre-moistened Hemorrhoidal/Vaginal Pads with Witch Hazel
- Provides Temporary Relief of Burning, Itching and Local Discomfort Associated with Hemorrhoids

100 MEDICATED PADS
SAFEWAY
For your protection, jar is sealed. Remove lid. If seal is broken or missing, do not use.
DISTRIBUTED BY SAFEWAY INC.
PO BOX 99, PLEASANTON, CA 94566-0009
This product is not manufactured or distributed by Parke-Davis, owner of the registered trademark TUCKS® Medicated Pads.